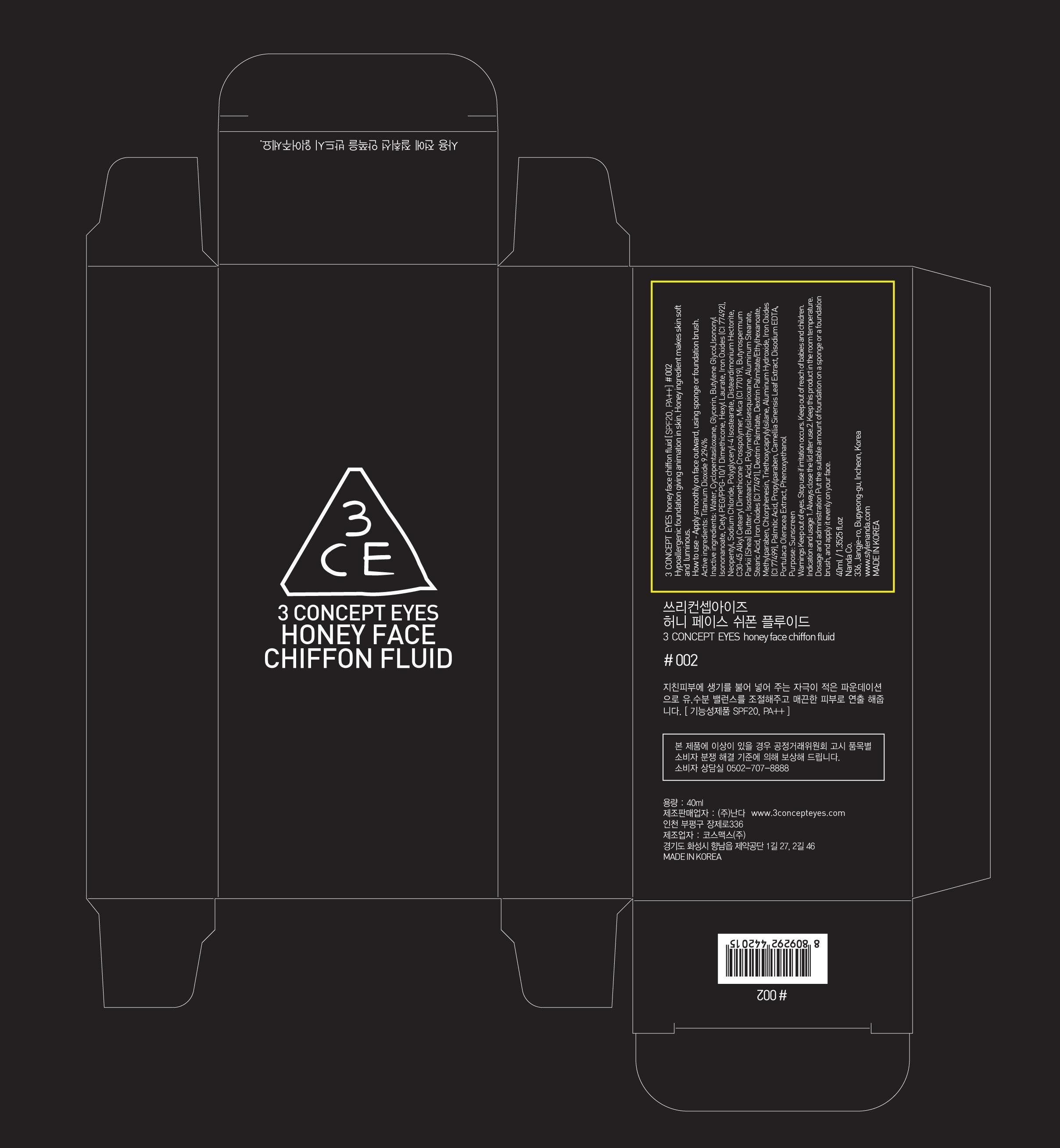 DRUG LABEL: 3 CONCEPT EYES HONEY FACE CHIFFON FLUID 002
NDC: 60764-006 | Form: CREAM
Manufacturer: NANDA CO., LTD.
Category: otc | Type: HUMAN OTC DRUG LABEL
Date: 20131003

ACTIVE INGREDIENTS: Titanium Dioxide 3.71 mg/40 mL
INACTIVE INGREDIENTS: Water; Glycerin

ACTIVE INGREDIENT

Active ingredients: Titanium Dioxide 9.294%

INACTIVE INGREDIENT

Inactive ingredients: Water, Cyclopentasiloxane, Glycerin, Butylene Glycol, Isononyl Isononanoate, Iron Oxides (CI 77492), Cetyl PEG/PPG-10/1 Dimethicone,Hexyl Laurate, Neopentyl Glycol Diethylhexanoate, Sodium Chloride, Polyglyceryl-4 Isostearate, Disteardimonium Hectorite, C30-45 Alkyl Cetearyl Dimethicone Crosspolymer, Butyrospermum Parkii (Shea) Butter, Isostearic Acid, Polymethylsilsesquioxane, Aluminum Stearate, Stearic Acid, Iron Oxides (CI 77491), Dextrin Palmitate, Dextrin Palmitate/Ethylhexanoate, Methylparaben, Chlorphenesin, Triethoxycaprylylsilane, Aluminum Hydroxide, Iron Oxides (CI 77499), Palmitic Acid, Propylparaben, Mica (CI 77019), Camellia Sinensis Leaf Extract, Disodium EDTA, Portulaca Oleracea Extract, Phenoxyethanol

PURPOSE

Purpose: Sunscreen

WARNINGS

Warnings Keep out of eyes. Stop use if irritation occurs. Keep out of reach of babies and children.

KEEP OUT OF REACH OF CHILDREN

Keep out of reach of babies and children.

INDICATIONS AND USAGE

Indication and usage 1. Always close the lid after use.2. Keep this product in the room temperature.

Dosage and administration Put the suitable amount of foundation on a sponge or a foundation brush, and apply it evenly on your face.